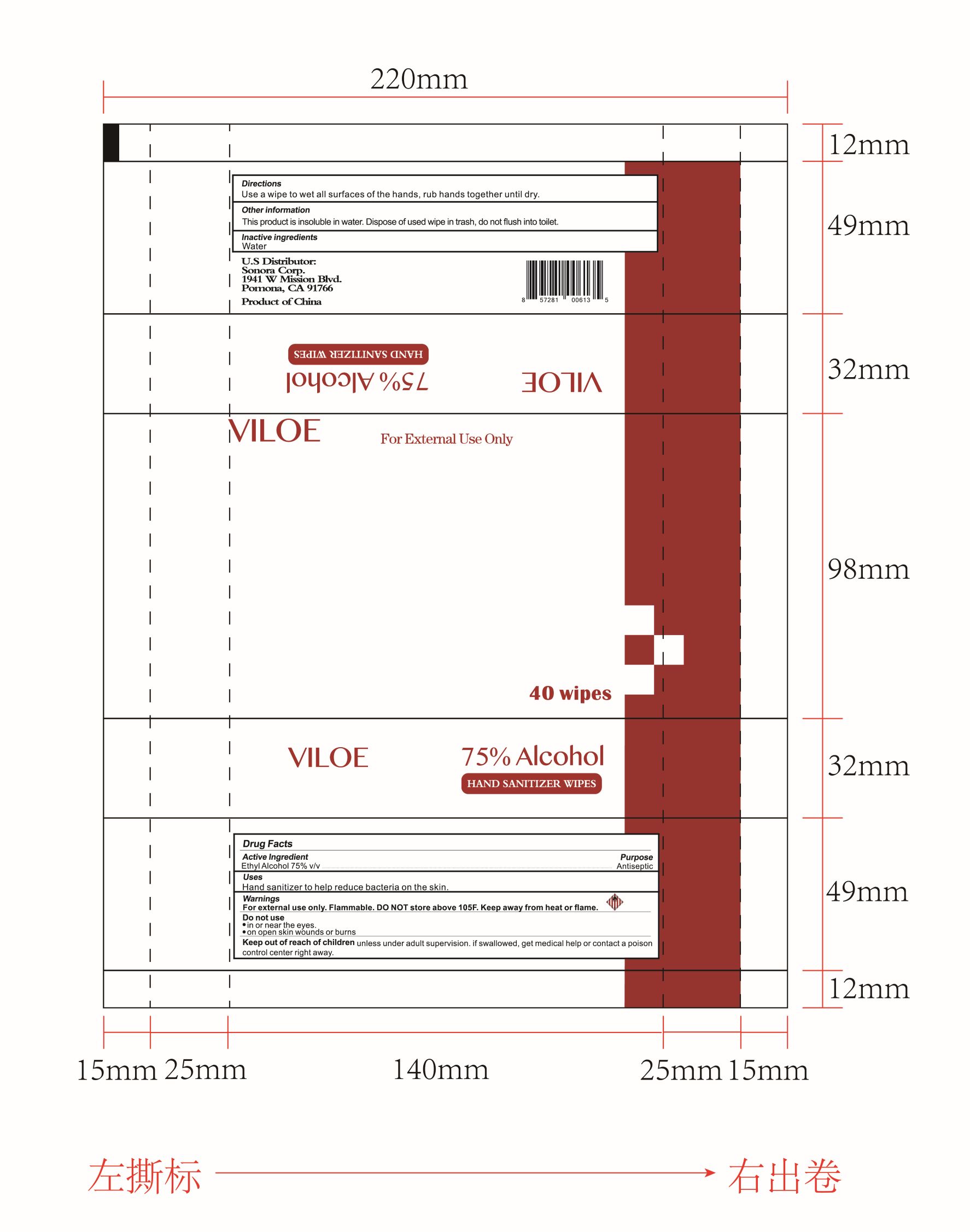 DRUG LABEL: 75% Alcohol HAND SANITIZER WIPES
NDC: 40562-017 | Form: CLOTH
Manufacturer: Anhui Hanbon Daily Chemical Co., Ltd.
Category: otc | Type: HUMAN OTC DRUG LABEL
Date: 20220105

ACTIVE INGREDIENTS: ALCOHOL 75 mL/100 mL
INACTIVE INGREDIENTS: WATER

Hanbon
75% Alcohol HAND SANITIZER WIPES
40PCS 40562-017-01

Active Ingredient(s)

Ethyl Alcohol 75% v/v

Purpose

Antiseptic

Use

Hand sanitizer to help reduce bacteria on the skin.

Warnings

- For external use only.
- Flammable. DO NOT store above 105℉.
- Keep awav from heat or flame.

DO NOT USE

- in or near the eyes.
- on open skin wounds or burns.

Keep out of reach of children unless under adult supervision. if swallowed, get medical help or contact a poison control center right away.

OTHER SAFETY INFORMATION

This product is insoluble in water. Dispose of used wipe in trash, do not flush into toilet.

Directions

Use a wipe to wet all surfaces of the hands, rub hands together until dry.

Inactive ingredients

Water

Package Label - Principal Display Panel

40 PATCH in 1 PACKET NDC: 40562-017-01